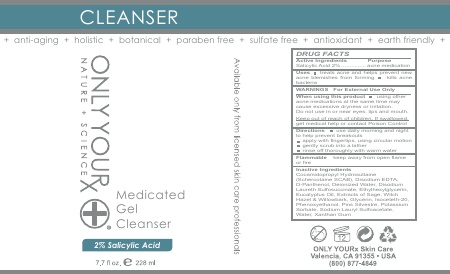 DRUG LABEL: Medicated Gel Cleanser -2% Salicylic Acid
NDC: 70367-008 | Form: SOAP
Manufacturer: Only Yourx, Inc.
Category: otc | Type: HUMAN OTC DRUG LABEL
Date: 20200123

ACTIVE INGREDIENTS: SALICYLIC ACID 2 g/100 mL
INACTIVE INGREDIENTS: DEXPANTHENOL; ETHYLHEXYLGLYCERIN; EUCALYPTUS OIL; XANTHAN GUM; MAGNESIUM DISODIUM EDTA; COCAMIDOPROPYL HYDROXYSULTAINE; DISODIUM LAURETH SULFOSUCCINATE; SAGE OIL; SODIUM LAURYL SULFOACETATE; WITCH HAZEL; WILLOW BARK; GLYCERIN; ISOCETETH-20; PHENOXYETHANOL; PINE NEEDLE OIL (PINUS SYLVESTRIS); POTASSIUM SORBATE; WATER

Active Ingredient: Salicylic Acid (2%)

INACTIVE INGREDIENT

Other Ingredients: Cocamidopropyl Hydrosultaine (Scherctaine SCAB), Disodium EDTA, D-Panthenol, Deionized Water, Disodium Laureth Sulfosuccinate, Ethylhexylglycerin, Eucalyptus Oil, Sage Extract, Witch Hazel, Willow Bark, Glycerin, Isoceteth-20, Phenoxyethanol, Pinus Sylvestre, Potassium Sorbate, Sodium Lauryl Sulfoacetate, Water, Xanthan Gum

DOSAGE AND ADMINISTRATION

Recommended Use: Use daily both morning and night. Cleanse facial and neck area by massaging a liberal amount onto damp skin using upward circular motions. Rinse thoroughly with warm water.

INDICATIONS AND USAGE

To cleanse skin and prevent acne

WARNINGS

WARNING: For External Use Only

Keep out of reach of children. If swallowed, seek medical help or contact a Poison Control Center.

When using this product: using other acne medications at the same time may cause excessive dryness or irritation. Do not use in or near eyes, lips and mouth.

Purpose: acne medication